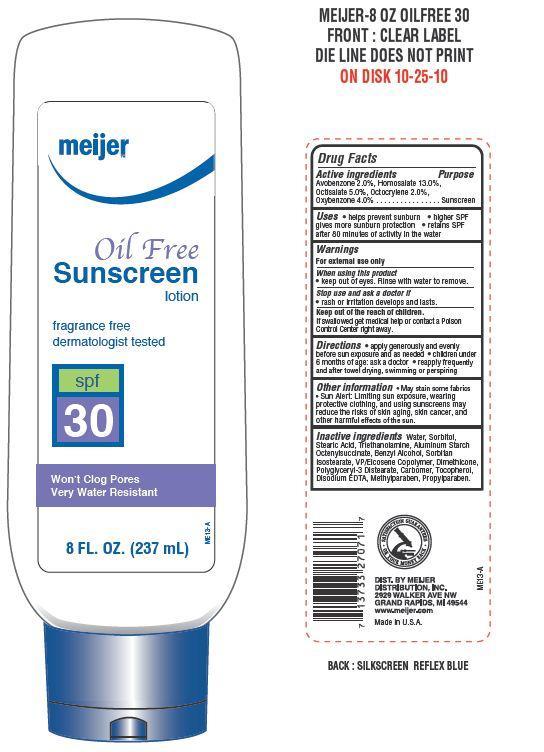 DRUG LABEL: Meijer Oil Free SPF 30
NDC: 41250-033 | Form: LOTION
Manufacturer: Meijer Distribution Inc
Category: otc | Type: HUMAN OTC DRUG LABEL
Date: 20130701

ACTIVE INGREDIENTS: AVOBENZONE 2 g/100 g; HOMOSALATE 13 g/100 g; OCTISALATE 5 g/100 g; OCTOCRYLENE 2 g/100 g; OXYBENZONE 4 g/100 g
INACTIVE INGREDIENTS: WATER; SORBITOL; STEARIC ACID; TROLAMINE; ALUMINUM STARCH OCTENYLSUCCINATE; BENZYL ALCOHOL; SORBITAN ISOSTEARATE; DIMETHICONE; POLYGLYCERYL-3 DISTEARATE; TOCOPHEROL; EDETATE DISODIUM; METHYLPARABEN; PROPYLPARABEN

Drug Facts

Active ingredients

Avobenzone 2.0%

Homosalate 13.0%

Octisalate 5.0%

Octocrylene 2.0%

Oxybenzone 4.0%

Uses

- helps prevent suburn
- higher SPF gives more sunburn protection
- retains SPF after 80 minutes of activity in water

Warnings

For external use only

When using this product

- keep out of eyes. Rinse with water to remove

Stop use and ask a doctor if

- rash or irritation develops and lasts

KEEP OUT OF REACH OF CHILDREN

Keep out of the reach of children. If swallowed get medical help or contact a Poison Control Center right away.

Directions

- apply generously and evenly before sun exposure and as needed
- children under 6 months of age: ask a doctor
- reapply frequently and after towel drying, swimming or perspiring

Other information

- may stain some fabrics
- Sun Alert: Limiting sun exposure, wearing protective clothing, and using sunscreens may reduce the risks of skin aging, skin cancer and other harmful effects of the sun

Inactive ingredients

Water, Sorbitol, Stearic Acid, Triethanolamine, Aluminum Starch Octenylsuccinate, Benzyl Alcohol, Sorbitan Isostearate, VP/Eicosene Copolymer, Dimethicone, Polyglyceryl-3 Distearate, Carbomer, Tocopherol, Disodium EDTA, Methylparaben, Propylparaben.

Principal Display Panel

meijer

Oil Free

Sunscreen lotion

fragrance free

dermatologist tested

spf 30

Won't Clog Pores

very water resistant

8 FL. OZ. (237 mL)

Purpose

Sunscreen